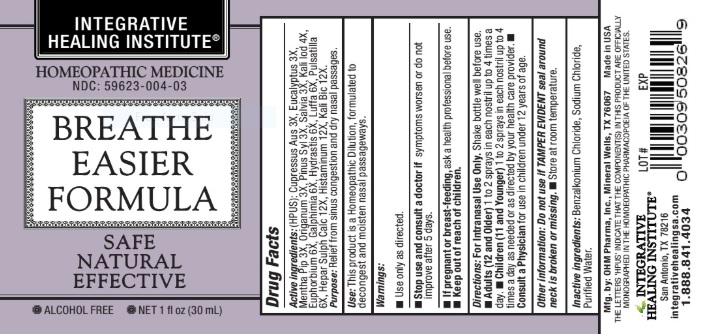 DRUG LABEL: Breathe Easier Formula

NDC: 59623-004 | Form: SPRAY
Manufacturer: Integrative Healing Institute, LLC
Category: homeopathic | Type: HUMAN OTC DRUG LABEL
Date: 20211229

ACTIVE INGREDIENTS: CUPRESSUS SEMPERVIRENS FRUITING LEAFY TWIG 3 [hp_X]/1 mL; EUCALYPTUS GLOBULUS LEAF 3 [hp_X]/1 mL; MENTHA PIPERITA 3 [hp_X]/1 mL; ORIGANUM MAJORANA WHOLE 3 [hp_X]/1 mL; PINUS SYLVESTRIS LEAFY TWIG 3 [hp_X]/1 mL; SAGE 3 [hp_X]/1 mL; POTASSIUM IODIDE 4 [hp_X]/1 mL; EUPHORBIA RESINIFERA RESIN 6 [hp_X]/1 mL; GALPHIMIA GLAUCA FLOWERING TOP 6 [hp_X]/1 mL; GOLDENSEAL 6 [hp_X]/1 mL; LUFFA OPERCULATA FRUIT 6 [hp_X]/1 mL; PULSATILLA VULGARIS 6 [hp_X]/1 mL; CALCIUM SULFIDE 12 [hp_X]/1 mL; HISTAMINE DIHYDROCHLORIDE 12 [hp_X]/1 mL; POTASSIUM DICHROMATE 12 [hp_X]/1 mL
INACTIVE INGREDIENTS: WATER; BENZALKONIUM CHLORIDE; SODIUM CHLORIDE

BREATHE EASIER FORMULA

ACTIVE INGREDIENT

Active ingredients: HPUS ingredients: Cupressus Aus 3X, Eucalyptus 3X, Mentha Pip 3X, Origanum 3X, Pinus Syl 3X, Salvia 3X, Kali Iod 4X, Euphorbium 6X, Galphimia 6X, Hydrastis 6X, Luffa 6X, Pulsatilla 6X, Hepar Sulph Calc 12X, Histaminum 12X, Kali Bic 12X.

PURPOSE

Purpose: Relief from sinus congestion and dry nasal passages.

INDICATIONS AND USAGE

Use: This product is a Homeopathic Dilution, formulated to decongest and moisten nasal passageways.

Warnings:

- Use only as directed.
- Stop use and consult a doctor if symptoms worsen or do not improve after 5 days.
- If pregnant or breast-feeding, ask a health professional before use.

- Keep out of reach of children.

DOSAGE AND ADMINISTRATION

Directions: For Intranasal Use Only. Shake bottle well before use.

- Adults (12 and Older) Spray 1 to 2 metered sprays into each nostril up to 4 times a day.
- Children (11 and Younger) Spray 1 to 2 metered sprays into each nostril up to 4 times a day as needed or as directed by your health care provider.
- Consult a Physician for use in children under 12 years of age.

Other information: Do not use if TAMPER EVIDENT seal around neck is broken or missing.

- Store at room temperature.

INACTIVE INGREDIENT

Inactive ingredients: Benzalkonium Chloride, Sodium Chloride, Purified Water.

OTHER SAFETY INFORMATION

Mfg. by: OHM Pharma, Inc., Mineral Wells, TX 76067

Made in USA

QUESTIONS

INTEGRATIVE HEALING INSTITUTE

San Antonio, TX 78216

integrativehealingsa.com

1.888.841.4034

PACKAGE LABEL

INTEGRATIVE HEALING INSTITUTE

- HOMEOPATHIC MEDICINE

- NDC: 59623-004-03

BREATHE EASIER FORMULA

- SAFE
- NATURAL
- EFFECTIVE

- ALCOHOL FREE
- NET 1 fl oz (30 mL)